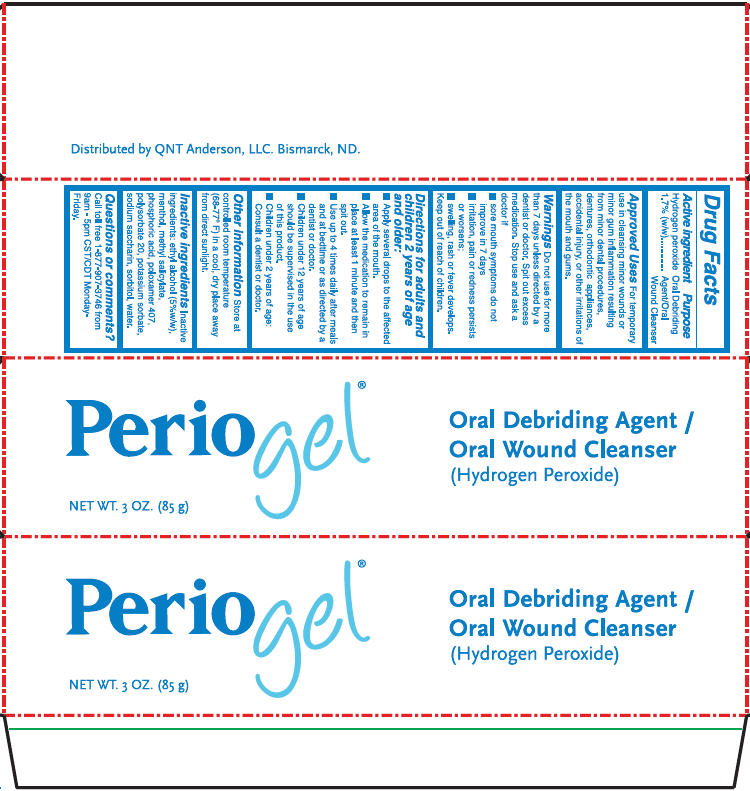 DRUG LABEL: Periogel
NDC: 75908-017 | Form: GEL
Manufacturer: QNT Anderson, LLC
Category: otc | Type: HUMAN OTC DRUG LABEL
Date: 20220513

ACTIVE INGREDIENTS: hydrogen peroxide 17 mg/1 g
INACTIVE INGREDIENTS: alcohol 50 mg/1 g; menthol, unspecified form; methyl salicylate; phosphoric acid; poloxamer 407; polysorbate 20; potassium sorbate; saccharin sodium; sorbitol; water

Periogel®

Drug Facts

Active ingredient

Hydrogen peroxide 1.7% (w/w)

Purpose

Oral Debriding Agent/Oral Wound Cleanser

Approved Uses

For temporary use in cleansing minor wounds or minor gum inflammation resulting from minor dental procedures, dentures, orthodontic appliances, accidental injury, or other irritations of the mouth and gums.

Warnings

Do not use for more than 7 days unless directed by a dentist or doctor. Spit out excess medication.

Stop use and ask a doctor if

- sore mouth symptoms do not improve in 7 days
- irritation, pain or redness persists or worsens;
- swelling, rash or fever develops.

Keep out of reach of children.

Directions for adults and children 2 years of age and older

- Apply several drops to the affected area of the mouth.
- Allow medication to remain in place at least 1 minute and then spit out.
- Use up to 4 times daily after meals and at bedtime or as directed by a dentist or doctor.
- Children under 12 years of age should be supervised in the use of this product.
- Children under 2 years of age:
  Consult a dentist or doctor.

Other information

Store at controlled room temperature (68°-77°F) in a cool, dry place away from direct sunlight.

Inactive ingredients

Inactive ingredients: ethyl alcohol (5% w/w), menthol, methyl salicylate, phosphoric acid, poloxamer 407, polysorbate 20, potassium sorbate, sodium saccharin, sorbitol, water.

Questions or comments?

Call toll free 1-877-907-3746 from 9am - 5pm CST/CDT Monday-Friday.

PRINCIPAL DISPLAY PANEL - 85 g Tube Carton

Periogel®

Oral Debriding Agent /
Oral Wound Cleanser
(Hydrogen Peroxide)

NET WT. 3 OZ. (85 g)